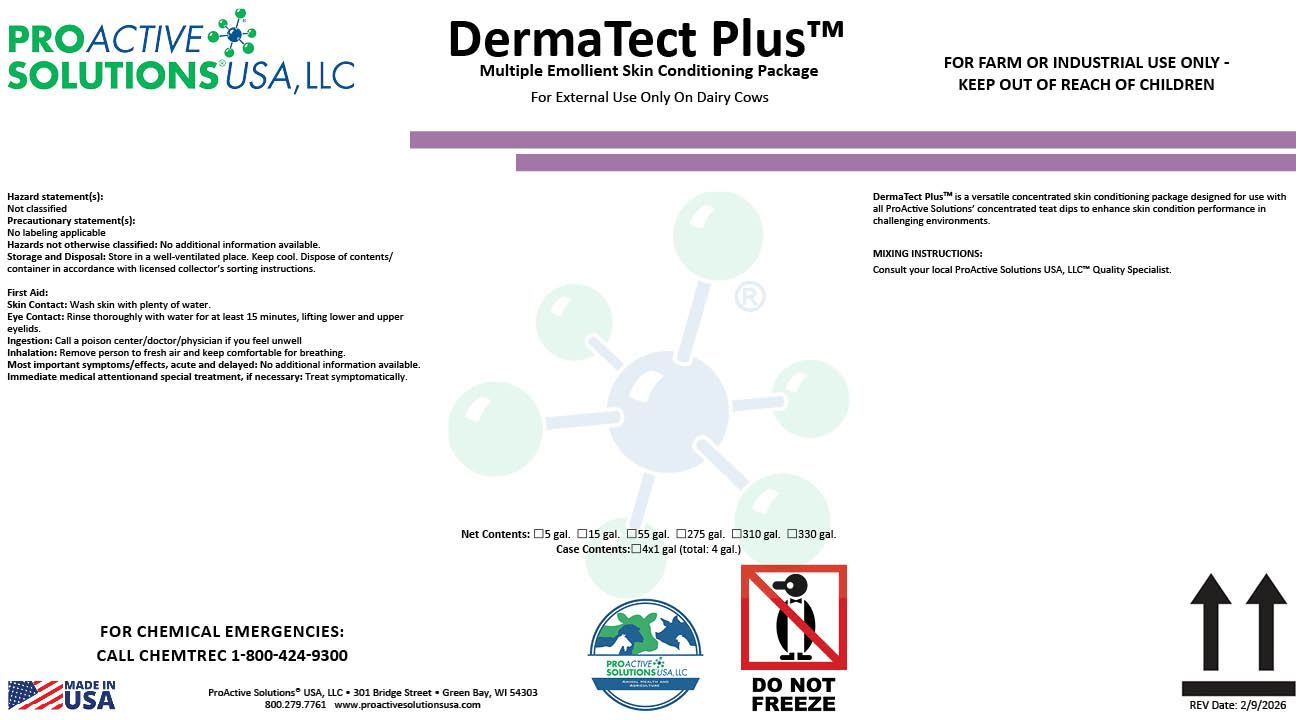 DRUG LABEL: DermaTect Plus
NDC: 63927-4141 | Form: SOLUTION
Manufacturer: ProActive Solutions USA LLC
Category: animal | Type: OTC ANIMAL DRUG LABEL
Date: 20260210

ACTIVE INGREDIENTS: GLYCERIN 29.91 kg/100 kg

DermaTect Plus

DermaTect Plus

DermaTect PlusTM is a versatile concentrated skin conditioning package designed for use with
all ProActive Solutions’ concentrated teat dips to enhance skin condition performance in
challenging environments.
MIXING INSTRUCTIONS:
Consult your local ProActive Solutions USA, LLC™ Quality Specialist.

Hazard statement(s):
Not classified
Precautionary statement(s):
No labeling applicable
Hazards not otherwise classified: No additional information available.
Storage and Disposal: Store in a well-ventilated place. Keep cool. Dispose of contents/
container in accordance with licensed collector’s sorting instructions.
First Aid:
Skin Contact: Wash skin with plenty of water.
Eye Contact: Rinse thoroughly with water for at least 15 minutes, lifting lower and upper
eyelids.
Ingestion: Call a poison center/doctor/physician if you feel unwell
Inhalation: Remove person to fresh air and keep comfortable for breathing.
Most important symptoms/effects, acute and delayed: No additional information available.
Immediate medical attentionand special treatment, if necessary: Treat symptomatically.